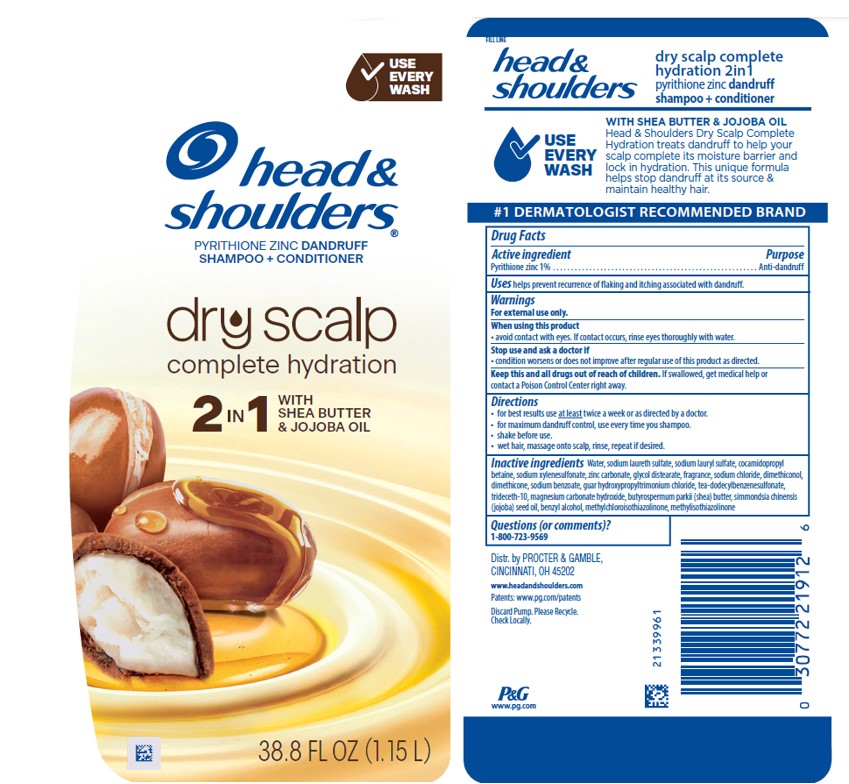 DRUG LABEL: Head and Shoulders Dry Scalp Complete Hydration 2in1
NDC: 84126-180 | Form: SHAMPOO
Manufacturer: The Procter & Gamble Manufacturing Company
Category: otc | Type: HUMAN OTC DRUG LABEL
Date: 20250922

ACTIVE INGREDIENTS: PYRITHIONE ZINC 1 g/100 mL
INACTIVE INGREDIENTS: SIMMONDSIA CHINENSIS (JOJOBA) SEED OIL; METHYLCHLOROISOTHIAZOLINONE; TRIETHANOLAMINE DODECYLBENZENESULFONATE; SODIUM LAURYL SULFATE; GUAR HYDROXYPROPYLTRIMONIUM CHLORIDE (1.7 SUBSTITUENTS PER SACCHARIDE); WATER; SODIUM LAURETH SULFATE; DIMETHICONE; ZINC CARBONATE; GLYCOL DISTEARATE; SODIUM XYLENESULFONATE; COCAMIDOPROPYL BETAINE; SODIUM CHLORIDE; SODIUM BENZOATE; MAGNESIUM CARBONATE HYDROXIDE; BUTYROSPERMUM PARKII (SHEA) BUTTER; DIMETHICONOL (50000 CST); TRIDECETH-10; BENZYL ALCOHOL; METHYLISOTHIAZOLINONE

Head and Shoulders Dry Scalp Complete Hydration 2in1

Drug Facts

Active ingredient

Pyrithione zinc 1%

Purpose

Anti-dandruff

Uses

helps prevent recurrence of flaking and itching associated with dandruff.

Warnings

For external use only.

When using this product

- avoid contact with eyes. If contact occurs, rinse eyes thoroughly with water.

Stop use and ask a doctor if

- condition worsens or does not improve after regular use of this product as directed.

KEEP OUT OF REACH OF CHILDREN

Keep this and all drugs out of reach of children. If swallowed, get medical help or contact a Poison Control Center right away.

Directions

- for best results use at least twice a week or as directed by a doctor.
- for maximum dandruff control, use every time you shampoo.
- shake before use.
- wet hair, massage onto scalp, rinse, repeat if desired.

Inactive ingredients

Water, sodium laureth sulfate, sodium lauryl sulfate, cocamidopropyl betaine, sodium xylenesulfonate, zinc carbonate, glycol distearate, fragrance, sodium chloride, dimethiconol, dimethicone, sodium benzoate, guar hydroxypropyltrimonium chloride, tea-dodecylbenzenesulfonate, trideceth-10, magnesium carbonate hydroxide, butyrospermum parkii (shea) butter, simmondsia chinensis (jojoba) seed oil, benzyl alcohol, methylchloroisothiazolinone, methylisothiazolinone

Questions (or comments)?

1-800-723-9569

MADE IN U.S.A. of U.S. and/or Imported Ingredients

Dist. by PROCTER & GAMBLE,
CINCINNATI, OH 45202

PRINCIPAL DISPLAY PANEL - 1.15L Bottle Label

head &
shoulders ®

PYRITHIONE ZINC DANDRUFF

SHAMPOO + CONDITIONER

DRY SCALP

CARE

complete hydration

2in1 WITH SHEA BUTTER

& JOJOBA OIL

38.8 FL OZ (1.15L)